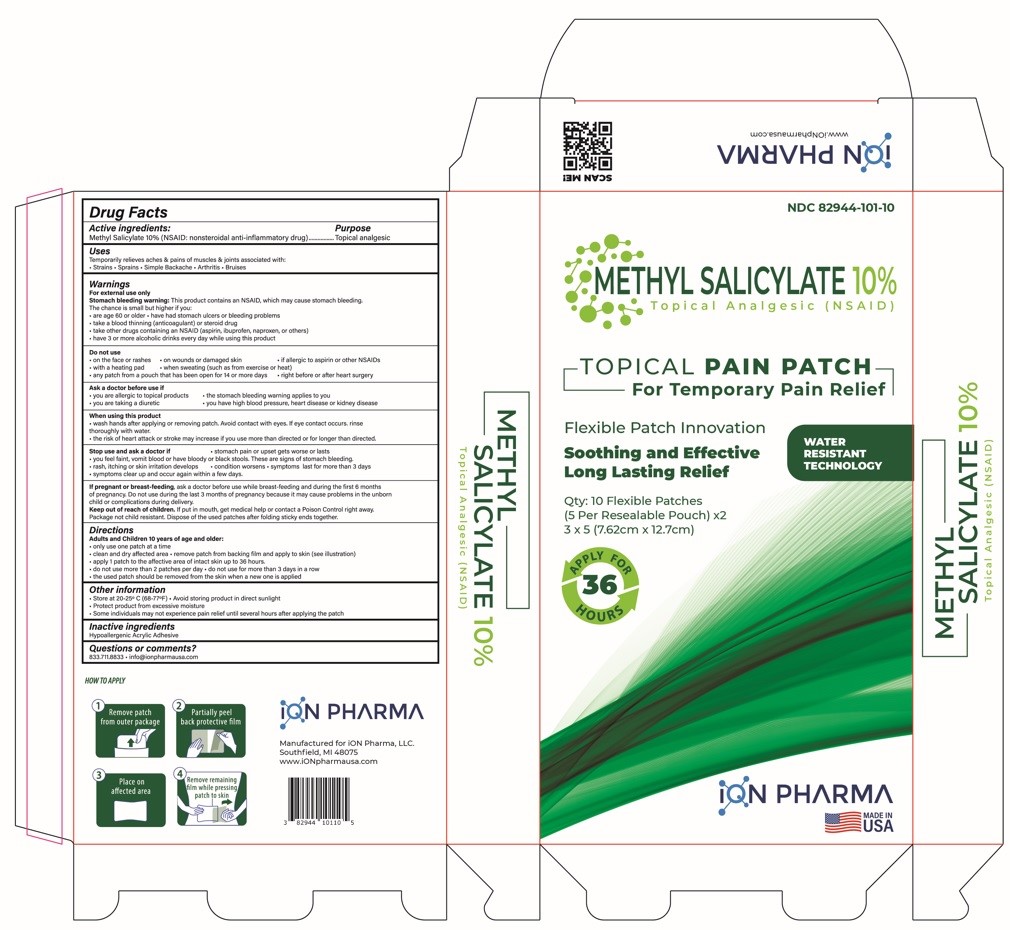 DRUG LABEL: Methyl Salicylate 10%
NDC: 82944-101 | Form: PATCH
Manufacturer: ION PHARMA, LLC
Category: otc | Type: HUMAN OTC DRUG LABEL
Date: 20240910

ACTIVE INGREDIENTS: METHYL SALICYLATE 10 g/1 1
INACTIVE INGREDIENTS: ACRYLIC ACID

Methyl Salicylate 10% Patch

Drug Facts

Active ingredients:

Methyl Salicylate 10% (NSAID: nonsteroidal anti-inflammatory drug)

Purpose

Topical analgesic

Uses

Temporarily relieves aches & pains of muscles & joints associated with:

- Strains
- Sprains
- Simple Backache
- Arthritis
- Bruises

Warnings

For external use only

Stomach bleeding warning:This product contains an NSAID, which may cause stomach bleeding.

The chance is small but higher if you:

- are age 60 or older
- have had stomach ulcers or bleeding problems
- take a blood thinning (anticoagulant) or steroid drug
- take other drugs containing as NSAID (aspirin, ibuprofen, naproxen, or others)
- have 3 or more alcoholic drinks every day while using this product

Do not use

- on the face or rashes
- on wounds or damaged skin
- if allergic to aspirin or other NSAIDs
- with a heating pad
- when sweating (such as from exercise or heat)
- any patch from a pouch that has been open for 14 or more days
- right before or after heat surgery

Ask a doctor before use if

- you are allergic to topical products
- the stomach bleeding warning applies to you
- you are taking a diuretic
- you have high blood pressure, heart disease or kidney disease

When using this product

- wash hands after applying or removing patch. Avoid contact with eyes. If eye contact occurs, rinse thoroughly with the water.
- the risk of heart attack or stroke may increase if you use more than directed or for longer than directed.

Stop use and ask a doctor if

- stomach pain or upset gets worse or lasts
- you feel faint, vomit blood or have bloody or black stools, These are signs of stomach bleeding.
- rash, itching or skin irritation develops
- condition worsens
- symptoms last for more than 3 days
- symptoms clear up and occur again within a few days.

PREGNANCY OR BREAST FEEDING

If pregnant or breast-feeding,ask a doctor before use while breast-feeding and during the first 6 months of pregnancy. Do not use during the last 3 months of pregnancy because it may cause problems in the unborn child or complications during delivery.

Keep out of reach of children.if put in mouth, get medical help or contact a Poison Control right away. Package not child resistant. Dispose of the used patches after folding sticky ends together.

Directions

Adults and Children 10 years of age and older:

- only use one patch at a time
- clean and dry affected area
- remove patch from backing film and apply to skin (see illustration)
- apply 1 patch to the affective area of intact skin up to 36 hours.
- do not use more than 2 patches per day
- do not use for more than 3 days in a row
- the used patch should be removed from the skin when a new one is applied

Other information

- Store at 20-25°C (68-77°F)
- Avoid storing product in direct sunlight
- Protect product from excessive moisture
- Some individuals may not experience pain relief until several hours after applying the patch

Inactive ingredients

Hypoallergenic Acrylic Adhesive

Questions or comments?

833.711.8833

- info@ionpharmausa.com

PRINCIPAL DISPLAY PANEL

NDC 82944-101-10

METHYL SALICYLATE 10%
Topical Analgesic (NSAID)

TOPICAL PAIN PATCH

For Temporary Pain Relief

Flexible Patch Innovation

Soothing and Effective
Long Lasting Relief

WATER
RESISTANT
TECHNOLOGY

Qty: 10 Flexible Patches
(5 Per Resealable Pouch) x2
3 x 5 (7.62cm x 12.7cm)

APPLY FOR 36 HOURS

ION PHARMA
MADE IN
USA